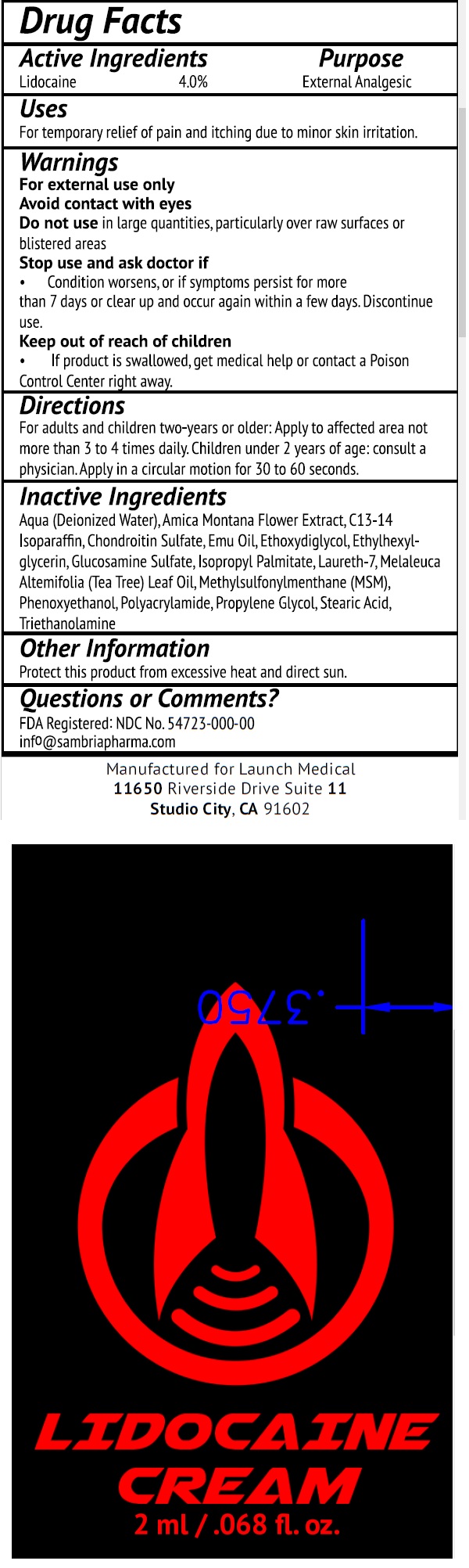 DRUG LABEL: Lidocaine
NDC: 54723-200 | Form: CREAM
Manufacturer: Sambria Pharmaceuticals Inc.
Category: otc | Type: HUMAN OTC DRUG LABEL
Date: 20231031

ACTIVE INGREDIENTS: LIDOCAINE 40 mg/1 mL
INACTIVE INGREDIENTS: WATER; ARNICA MONTANA FLOWER; C13-14 ISOPARAFFIN; EMU OIL; DIETHYLENE GLYCOL MONOETHYL ETHER; ETHYLHEXYLGLYCERIN; GLUCOSAMINE SULFATE; ISOPROPYL PALMITATE; LAURETH-7; TEA TREE OIL; DIMETHYL SULFONE; PHENOXYETHANOL; PROPYLENE GLYCOL; STEARIC ACID; TROLAMINE

Lidocaine Cream

Active Ingredients

Lidocaine 4.0%

Purpose

External Analgesic

Uses

For temporary relief of pain and itching due to minor skin irritation.

Warnings

For external use only

Avoid contact with eyes

Do not use

in large quantities, particularly over raw surfaces or blistered areas

Stop use and ask doctor if

- Condition worsens, or if symptoms persist for more than 7 days or clear up and occur again within a few days. Discontinue use.

Keep out of reach of children

If product is swallowed, get medical help or contact a Poison Control Center right away.

Directions

For adulst and children two-years or older: Apply to affected area not more than 3 to 4 times daily. Children under 2 years of age: consult a physician. Apply in a circular motion for 30 to 60 seconds.

Inactive Ingredients

Aqua (Deionized Water), Arnica Montana Flower Extract, C13-14 Isoparaffin, Chondroitin Sulfate, Emu Oil, Ethoxydiglycol, Ethylhexylglycerin, Glucosamine Sulfate, Isopropyl Palmitate, Laureth-7, Melaleuca Alternifolia (Tea Tree) Leaf Oil, Methylsulfonylmethane (MSM), Phenoxyethanol, Polyacrylamide, Propylene Glycol, Stearic Acid, Triethanolamine

Other Information

Protect this product from excessive heat and direct sun.

Questions or Comments?

FDA Registered: NDC No. 54723-000-00 info@sambriapharma.com